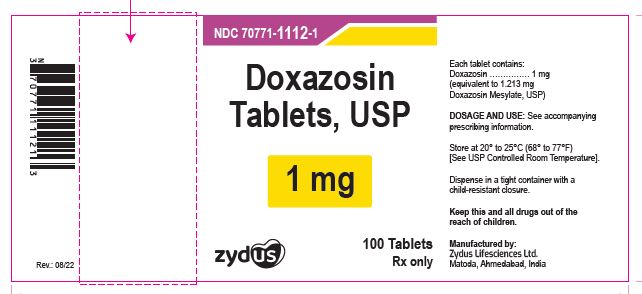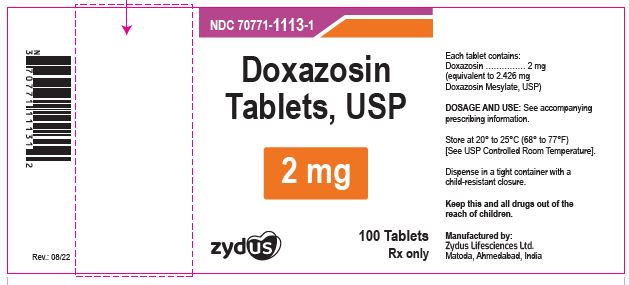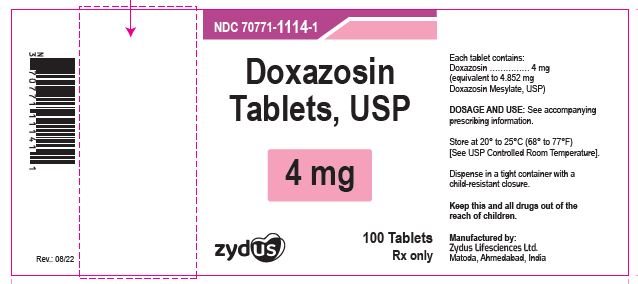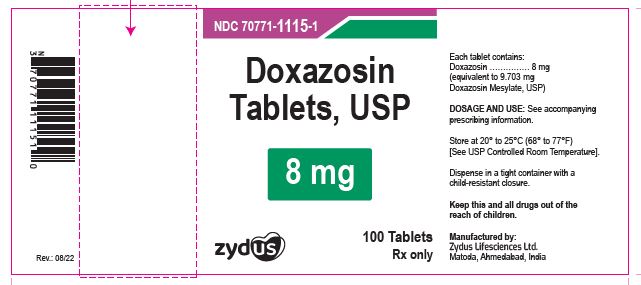 DRUG LABEL: Doxazosin
NDC: 70771-1112 | Form: TABLET
Manufacturer: Zydus Lifesciences Limited
Category: prescription | Type: HUMAN PRESCRIPTION DRUG LABEL
Date: 20241128

ACTIVE INGREDIENTS: DOXAZOSIN MESYLATE 1 mg/1 1
INACTIVE INGREDIENTS: CELLULOSE, MICROCRYSTALLINE; LACTOSE MONOHYDRATE; MAGNESIUM STEARATE; SODIUM LAURYL SULFATE; SODIUM STARCH GLYCOLATE TYPE A POTATO

DOXAZOSIN TABLETS

PACKAGE LABEL.PRINCIPAL DISPLAY PANEL

NDC 70771-1112-1 in bottle of 100 Tablets

Doxazosin Tablets USP, 1 mg

Rx only

100 Tablets

NDC 70771-1113-1 in bottle of 100 Tablets

Doxazosin Tablets USP, 2 mg

Rx only

100 Tablets

NDC 70771-1114-1 in bottle of 100 Tablets

Doxazosin Tablets USP, 4 mg

Rx only

100 Tablets

NDC 70771-1115-1 in bottle of 100 Tablets

Doxazosin Tablets USP, 8 mg

Rx only

100 Tablets